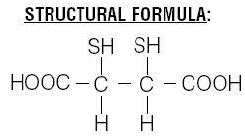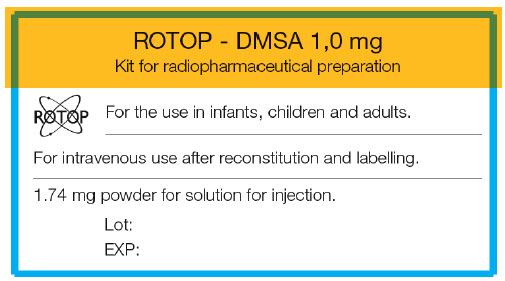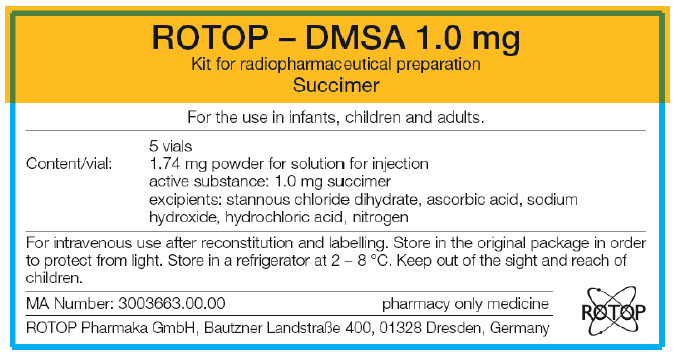 DRUG LABEL: ROTOP - DMSA
NDC: 71647-001 | Form: INJECTION, POWDER, LYOPHILIZED, FOR SOLUTION
Manufacturer: ROTOP Pharmaka GmbH
Category: prescription | Type: HUMAN PRESCRIPTION DRUG LABEL
Date: 20210309

ACTIVE INGREDIENTS: 2,3-DIMERCAPTOSUCCINIC ACID 1 mg/1 1
INACTIVE INGREDIENTS: STANNOUS CHLORIDE; ASCORBIC ACID; SODIUM HYDROXIDE; HYDROCHLORIC ACID; NITROGEN

ROTOP – DMSA 1.0 mg

HEALTH CARE PROVIDER LETTER

THERAGNOSTICS

Theragnostics Inc.
150 Grossman Drive, Suite 306
Braintree, MA 02184

IMPORTANT ORDERING INFORMATION

December 1, 2020

Subject: New Ordering Procedures for ROTOP DMSA Kit for the Preparation of Technetium Tc99m Succimer Injection

Dear Healthcare Professional,

Please note the following information prior to placing an order for ROTOP DMSA Kit for the Preparation of Technetium Tc99m Succimer Injection. On September 1, 2020, GE Healthcare sold their radiopharmacy chain to a third party, Radioisotope Life Sciences (RLS), and no longer have the capability to make radiolabelled 99mTc-DMSA.

To place an order for ROTOP DMSA Kit for the Preparation of Technetium Tc99m Succimer Injection (Theragnostics), please contact your local nuclear pharmacy, ex. Cardinal Health, Jubilant, RLS, UPPI, Pharmalogic or another independent nuclear pharmacy. You can also contact Medi-Physics Inc., dba GE Healthcare, 1-800-292-8514, 8:00 AM to 6:30 PM Eastern time; or via web portal address ci.gehealthcare.com/us.

CONTACT NUMBERS: Please use the following contact numbers as appropriate:
Phone: 1-617-286-7479
Fax: 1-617-398-6337

Sincerely,

Gregory Mullen
President & CEO

HEALTH CARE PROVIDER LETTER

THERAGNOSTICS

Theragnostics Inc.
150 Grossman Drive, Suite 306
Braintree, MA 02184

IMPORTANT PRESCRIBING INFORMATION

December 1, 2020

Subject: Temporary importation of Kit for the Preparation of Technetium Tc99m Succimer Injection to address drug shortage issues

Dear Healthcare Professional,

Due to the current critical shortage of DMSA Kit for the Preparation of Technetium Tc99m Succimer, Theragnostics Inc. (Theragnostics) is coordinating with the U.S. Food and Drug Administration (FDA) to increase the availability of the drug. Theragnostics has initiated temporary importation of DMSA Kit for the Preparation of Technetium Tc99m Succimer Injection into the U.S. market. This product is marketed in Germany and is manufactured in Dresden, Germany by ROTOP Pharmaka GmbH for Theragnostics.

At this time, no other entity except ROTOP Pharmaka GmbH, Germany through its US Agent, Theragnostics, and Theragnostics' distributor, Medi-Physics Inc., dba GE Healthcare, is authorized by the FDA to import or distribute the DMSA Kit for the Preparation of Technetium Tc99m Succimer Injection in the U.S. FDA has not approved ROTOP Pharmaka GmbH's Kit for DMSA Preparation of Technetium Tc99m Succimer Injection product in the U.S.

Effective immediately, and during this temporary period, Theragnostics will offer the following presentation of ROTOP DMSA Kit for the Preparation of Technetium Tc99m Succimer Injection:

Product | Strength | Size | Marketing Authorization #
ROTOP DMSA (Kit for the Preparation of Technetium Tc99m Succimer Injection) | One vial contains 1.74 mg powder with the active substance: 1.0 mg succimer | 5 vials in a carton | 3003663.00.00 Germany (NDC 71647-001-01)

The vial and carton labels will display the text, translated to English, as approved via the Marketing Authorization of EEA in Germany. At the end of this letter you will find a product comparison table with the prescribing information in English, as well as images of the labels for your reference.

There are some differences in the labeling between the FDA-approved DMSA Kit for the Preparation of Technetium Tc99m Succimer Injection (GE Healthcare) product and ROTOP DMSA Kit for the Preparation of Technetium Tc99m Succimer Injection (Theragnostics) product (please see the product comparison tables below). These differences do not alter the favorable risk/benefit of the drug:

- In alignment with current practice, the ROTOP DMSA Kit for the Preparation of Technetium Tc99m Succimer label does not include a statement under the heading "Pediatric Use" that appears in the GE Healthcare label as follows: "Safety and effectiveness in pediatric patients have not been established."
- Unlike the GE Healthcare label, the ROTOP DMSA Kit for the Preparation of Technetium Tc99m Succimer label contains pediatric dosing information under the heading "How to Use ROTOP DMSA". Pediatric doses can also be calculated online through the Society of Nuclear Medicine and Molecular Imaging website's Pediatric Injected Activity Tool.
- The ROTOP DMSA Kit for the Preparation of Technetium Tc99m Succimer label does not state the product is sterile; however, like the GE Healthcare product, ROTOP DMSA Kit for the Preparation of Technetium Tc99m Succimer is manufactured to be sterile.
- Side effects encountered with use of the ROTOP DMSA Kit for the Preparation of Technetium Tc99m Succimer within the U.S. can be reported directly to Theragnostics, Inc., at 1-888-286-3848 rather than the foreign site referenced in the label for ROTOP DMSA Kit for the Preparation of Technetium Tc99m Succimer.

ROTOP DMSA Kit for the Preparation of Technetium Tc99m Succimer Injection is available only by prescription in the U.S.

Please refer to the package insert for the FDA-approved DMSA Kit for the Preparation of Technetium Tc99m Succimer drug product for full prescribing information.

ROTOP DMSA Kit for the Preparation of Technetium Tc99m Succimer Injection (Theragnostics) does not contain a barcode. Institutions should manually input the product into their systems. Alternative procedures should be followed to assure that the correct drug product is being used and administered to individual patients.

If you have any questions about the information contained in this letter or the use of ROTOP DMSA Kit for the Preparation of Technetium Tc99m Succimer Injection (Theragnostics), please contact Theragnostics, Inc., Braintree, Massachusetts, 1-617-286-7479, 9:00 AM to 5:00 PM Eastern time.

Please note the following information prior to placing an order for ROTOP DMSA Kit for the Preparation of Technetium Tc99m Succimer Injection (Theragnostics). On September 1, 2020, GE Healthcare sold their radiopharmacy chain to a third party, Radioisotope Life Sciences (RLS), and no longer have the capability to make radiolabelled 99mTc-DMSA.

To place an order for ROTOP DMSA Kit for the Preparation of Technetium Tc99m Succimer Injection (Theragnostics), please contact your local nuclear pharmacy, ex. Cardinal Health, Jubilant, RLS, UPPI, Pharmalogic or another independent nuclear pharmacy. You can also contact Medi-Physics Inc., dba GE Healthcare, 1-800-292-8514, 8:00 AM to 6:30 PM Eastern time; or via web portal address ci.gehealthcare.com/us.

To report adverse events or quality problems associated with the use of this product, please call Theragnostics, Inc., Braintree, Massachusetts, 1-888-286-3848

CONTACT NUMBERS: Please use the following contact numbers as appropriate:
Phone: 1-617-286-7479
Fax: 1-617-398-6337

Adverse reactions or quality problems experienced with the use of this product may be reported to the FDA's MedWatch Adverse Event Reporting program either online, by regular mail or by fax.

- Complete and submit the report Online: www.fda.gov/medwatch/report.htm
- Regular Mail or Fax: Download form www.fda.gov/MedWatch/getforms.htm or call 1-800-332-1088 to request a reporting form, then complete and return to the address on the pre-addressed form, or submit by fax to 1-800-FDA-0178 (1-800-332-0178)

Sincerely,

Gregory Mullen
President & CEO

Attachments:
1. Product Comparison Table
2. Label Comparison Table
3. Vial and Carton Labels

Attachment 1: Product Comparison Table

Comparison Table 1: Theragnostics vs. GE Healthcare Reference Product
Characteristics | Reference product: MPI DMSA KIDNEY REAGENT (Kit for the Preparation of Technetium Tc99m Succimer Injection) | Theragnostics' product: Kit for the Preparation of Technetium Tc99m Succimer Injection
Conditions of use | DMSA is indicated for the use as an aid in the scintigraphic evaluation of renal parenchymal disorders. | Theragnostics' Kit is indicated for the use as an aid in the scintigraphic evaluation of renal parenchymal disorders.
Active ingredient | meso-2,3-dimercaptosuccinic acid | meso-2,3-dimercaptosuccinic acid
Inactive ingredients | stannous chloride dihydrate | stannous chloride dihydrate
Inactive ingredients | ascorbic acid | ascorbic acid
Inactive ingredients | inositol | ---
Inactive ingredients | sodium hydroxide | sodium hydroxide
Inactive ingredients | hydrochloric acid | hydrochloric acid
Inactive ingredients | nitrogen | nitrogen
Route of Administration | Intravenous | Intravenous
Dosage form | Injection | Injection
Strength | N/A | N/A
Description | Each vial contains a sterile, pyrogen-free freeze-dried mixture of 1.0 mg dimercaptosuccinic acid, 0.42 mg stannous chloride dihydrate [0.38 mg (minimum) stannous chloride dihydrate (SnCl2 ∙2H2O) and 0.46 mg (maximum) total tin expressed as stannous chloride dihydrate (SnCl2 ∙2H2O)], 0.70 mg ascorbic acid, and 50.0 mg inositol. After freeze-drying, vials are sealed under a nitrogen atmosphere with a rubber closure. Sodium hydroxide and hydrochloric acid have been used for pH adjustment. When sterile, oxidant-free, pyrogen-free sodium pertechnetate Tc^99m injection in isotonic saline is combined with the vial contents, following the instructions provided with the kit, a complex is formed. After 10 minutes' incubation the reconstituted solution is ready for intravenous injection. | One vial contains 1.74 mg powder with the active substance, 1.0 mg succimer. The excipients are: stannous chloride dihydrate, ascorbic acid, sodium hydroxide, hydrochloric acid 36% and nitrogen.

Attachment 2: Labeling Comparison Table

GE REFERENCE PRODUCT INSERT |  |  |  |  |  |  |  |  |  | DIFFERENCES | ROTOP-DMSA INSERT
 |  |  |  |  |  |  |  |  |  | DMSA English translation note | This Package Leaflet and Summary of Product Characteristics was translated by the manufacturer based on the original German document (Vs. 4), authorized by the German Federal Institute for Drugs and Medicinal Services in November 2014.
 |  |  |  |  |  |  |  |  |  |  | Package Leaflet and Summary of Product Characteristics
DMSA Kit for the Preparation of Technetium Tc99m Succimer Injection |  |  |  |  |  |  |  |  |  | Product name specific for market | ROTOP - DMSA, 1.0 mg Kit for radiopharmaceutical preparation Succimer
DIAGNOSTIC - FOR INTRAVENOUS USE |  |  |  |  |  |  |  |  |  | Insert layout specific to manufacturer; GE layout adjusted to "line" up to sections with ROTOP insert for ease of review German product specific instructions |  | Read all of this leaflet carefully before you start using this medicine.; - Keep this leaflet. You may need to read it again. - If you have any further questions, ask your doctor or pharmacist. - This medicine has been prescribed for you. Do not pass it on to others. It may harm them, even if their symptoms are the same as yours. - If any of the side effects gets serious, or if you notice any side effects not listed in this leaflet, please tell your doctor or pharmacist.
 |  |  |  |  |  |  |  |  |  |  | In this leaflet:; 1. What ROTOP – DMSA is and what it is used for 2. Before you use ROTOP - DMSA 3. How to use ROTOP - DMSA 4. Possible side effects 5. How to store ROTOP - DMSA 6. Further information
DESCRIPTION Each vial contains a sterile, pyrogen-free freeze-dried mixture of 1.0 mg dimercaptosuccinic acid, 0.42 mg stannous chloride dihydrate [0.38 mg (minimum) stannous chloride dihydrate (SnCl2∙2H2O) and 0.46 mg (maximum) total tin expressed as stannous chloride dihydrate (SnCl2∙2H2O)], 0.70 mg ascorbic acid, and 50.0 mg inositol. After freeze-drying, vials are sealed under a nitrogen atmosphere with a rubber closure. Sodium hydroxide and hydrochloric acid have been used for pH adjustment. When sterile, oxidant-free, pyrogen-free sodium pertechnetate Tc^99m injection in isotonic saline is combined with the vial contents, following the instructions provided with the kit, a complex is formed. After 10 minutes incubation the reconstituted solution is ready for intravenous injection. Chemical Name: meso-2,3-dimercaptosuccinic acid The succimer component of DMSA consists of more than 90% meso isomer and less than 10% d,l isomer. |  |  |  |  |  |  |  |  |  | Insert layout and details specific to manufacturer | 1. WHAT ROTOP – DMSA IS AND WHAT IT IS USED FOR ROTOP - DMSA is a radiodiagnostic pharmaceutical. The kit contains the non-radioactive powder for reconstitution of the [99mTc]technetium succimer injection solution ([99mTc]-DMSA). The sodium [99mT]pertechnetat which is needed for the preparation is not part of this kit. After labelling with sodium [99mTc]technetium pertechnetat solution, ROTOP - DMSA is used for static renal scintigraphy when adequate diagnostics are not possible using other diagnostic procedures (such as ultrasound):; - to identify focal renal parenchymal changes (e.g. in the case of renal infarction) - to identify norm variants such as atypical double kidney, small kidney, dysplastic kidney, horseshoe kidney, as well as to identify ectopic kidneys - to confirm absence of renal function in multicystic kidneys.
PHYSICAL CHARACTERISTICS Technetium Tc99m decays by isomeric transition with a physical half-life of 6.02 hours^1. The principal photon that is useful for detection and imaging studies is listed in Table 1. |  |  |  |  |  |  |  |  |  | Insert layout and details specific to manufacturer
 |  | Table 1. Principal Radiation Emission Data^1 |  |  |  |  |  |  |  | Insert layout and details specific to manufacturer
 |  | Radiation |  | Mean % / Disintegration |  |  | Mean Energy (keV) |  |  | Insert layout and details specific to manufacturer
 |  | Gamma 2 |  | 89.07 |  |  | 140.5 |  |  | Insert layout and details specific to manufacturer
^1 Kocher, David C., "Radioactive Decay Data Tables," DOE/TIC-11026,108 (1981).
INDICATIONS AND USAGE DMSA is to be used as an aid in the scintigraphic evaluation of renal parenchymal disorders. PRECAUTIONS General As in the use of any radioactive material, care should be taken to minimize radiation exposure to the patient consistent with proper patient management and to ensure minimum radiation exposure to occupational workers. DMSA should be used between 10 minutes and 4 hours following reconstitution (see "Preparation" section). Any unused portion should be discarded after that time. Some patients with advanced renal failure may exhibit poor renal intake of Tc99m DMSA. It has been reported that satisfactory images may be obtained in some of these patients by delaying imaging for up to 24 hours. The contents of the kit vials are intended only for use in the preparation of DMSA Injection and are not to be directly administered to the patient. The contents of the kit vials are not radioactive. However, after Tc99m is added, adequate shielding of the final preparation must be maintained. Radiopharmaceuticals should be used only by physicians who are qualified by training and experience in the safe use and handling of radionuclides and whose experience and training have been approved by the appropriate government agency authorized to license the use of radionuclides. Carcinogenesis, Mutagenesis, Impairment of Fertility No long term animal studies have been performed to evaluate carcinogenic potential, mutagenic potential, or whether technetium Tc99m succimer injection affects fertility in males or females. Pregnancy Category C Animal reproduction studies have not been conducted with technetium Tc99m succimer injection. It is also not known whether technetium Tc99m succimer injection can cause fetal harm when administered to a pregnant woman or can affect reproduction capacity. Technetium Tc99m succimer injection should be administered to a pregnant woman only if clearly needed. Ideally, examinations using radiopharmaceuticals, especially those elective in nature, of a woman of child bearing capability should be performed during the first few (approximately 10) days following the onset of menses. Nursing Mothers Technetium Tc99m is excreted in human milk during lactation; therefore, formula feedings should be substituted for breast feedings. Pediatric Use Safety and effectiveness in pedriatric patients have not been established. Geriatric Use Clinical studies of DMSA did not include sufficient numbers of subjects age 65 and over to determine whether they respond differently from younger patients. Other reported clinical experience has not identified differences in responses between the elderly and younger patients. In general, dose selection for an elderly patient should be cautious usually starting at the low end of the dosing range, reflecting the greater frequency of decreased hepatic, renal or cardiac function, and of concomitant disease or other drug therapy. This drug is known to be substantially excreted by the kidney, and the risk of toxic reactions to this drug may be greater in patients with impaired renal function. Because elderly patients are more likely to have decreased renal function, care should be taken in dose selection, and it may be useful to monitor renal function. |  |  |  |  |  |  |  |  |  | Insert layout and details specific to manufacturer | 2. BEFORE YOU USE ROTOP - DMSA Take special care with ROTOP – DMSA ROTOP - DMSA is not suitable for determining global renal function from the DMSA accumulation. In the case of proximal tubulopathies [99mTc]DMSA does not lead to a sufficient diagnostic renal accumulation. The patient must be well hydrated before and after administration. In order to keep radiation exposure to a minimum, patients must be encouraged to empty their bladders as often as possible during the first hours after the examination. For each patient it should be carefully considered whether the expected diagnostic benefits outweigh the risk linked to radiation exposure. In order to keep the radiation dose as low as possible, the administered activity may not be higher than that required for eliciting the diagnostic information. Radiopharmaceuticals may be received, used and administered only by authorised persons in areas specially designated for this purpose. The manipulation and use of these products is subject to the regulations of the local supervisory authority and/or requires appropriate permission. Contraindications ROTOP-DMSA should not be used in case of hypersensitivity to the active substance or to any of the excipients listed in section 6. Using other medicines Chemotherapeutic agents such as methotrexate, cyclophosphamide and vincristine can alter the biodistribution of [99mTc]DMSA. Shifting the acid/base balance, e.g. through ammonium chloride or sodium hydrogen carbonate, effects in vivo a change in the valence of the [99mTc]DMSA complex and in turn a lower accumulation in the renal cortex with simultaneous strong accumulation in the liver and rapid urine excretion. Mannitol leads to dehydration and in turn to a reduction in the extraction of [99mTc]DMSA. In the case of renal artery stenosis, ACE inhibitors can lead to a reversible insufficiency of the tubular function and in turn to a reduced accumulation of [99mTc]DMSA as a result of the reduction in filtration pressure in the affected kidney. If high doses of other chelating agents are injected at the same time, the stability of the [99mTc]DMSA DMSA may be influenced, thus effecting a change in kinetics. Pregnancy and lacation Pregnancy: No data on the clinical use of [99mTc]DMSA with pregnant women is available. If it is necessary to administer a radiopharmaceutical product to a woman of child-bearing age, she must have a pregnancy test first. If a woman has missed a period, it must be assumed that she is pregnant. In case of doubt, radiation exposure must be reduced to the minimum amount required to acquire the needed clinical information. In this case, alternative investigative methods must be considered that do not use ionising radiation. Radiopharmaceutical examinations of pregnant women also expose the foetus to radiation. For this reason, [99mTc]DMSA may only be used if there is a vital indication and if the expected benefit outweighs the risk to mother and child. Lactation: Before administering [99mTc]DMSA to a breast-feeding mother, it must be considered whether the investigation could also be delayed until the mother has ceased breast-feeding and as to whether using a radiopharmaceutical is the most appropriate examination method, bearing in mind the secretion of activity into breast milk. If administering [99mTc]DMSA is deemed necessary, breast-feeding must be interrupted for at least 12 hours, and the expressed breast milk discarded.
 |  |  |  |  |  |  |  |  |  | Insert layout and details specific to manufacturer | Driving and using machines Effects on the ability to drive or use machines have not been described.
DOSAGE AND ADMINISTRATION The suggested dose range for slow I.V. administration to be employed in the average patient (70 kg) for renal parenchymal imaging is 74-222 MBq, 2-6 mCi technetium Tc99m succimer injection. The product must be used between 10 minutes to 4 hours following preparation (see "Preparation" section). Acceptable renal images may be obtained beginning 1 to 2 hours post injection. Any unused portion should be discarded after that time. The patient dose should be measured by a suitable radioactivity calibration system immediately prior to administration. Do not use after the expiration date stated on the label. The components of the kit are supplied sterile and pyrogen-free. Aseptic procedures normally employed in making additions and withdrawals from sterile, pyrogen-free containers should be used during addition of sodium pertechnetate Tc99m injection solutions and during the withdrawal of doses for patient administration. |  |  |  |  |  |  |  |  |  |  | Precautions for avoiding hazards for the environment Radiopharmaceuticals must be prepared and used by the user under precautions for the protection from ionizing radiation and taking pharmaceutical quality standards into account. In accordance with the guidelines for Good Pharmaceutical Manufacturing Practice, work must be done under aseptic conditions. Patients treated with radiopharmaceuticals pose a risk for other persons based on external radiation exposure or contamination due to spilling urine, vomiting, etc. For this reason, the precautionary measures provided by the national radiation protection regulations must be observed. Contamination brought about by radioactivity that has been excreted by the patient must be avoided. 3. HOW TO USE ROTOP - DMSA Single intravenous use after preparation with sodium [99mTc]pertechnetate solution. Adults are given 0.3 to 1.0 mg succimer and activities of 70 MBq. Scintigraphic examinations should not be carried out until at least 1 hour after application; waiting 3 hours is preferable. In the case of very poor renal function, waiting periods of up to 6 hours should be observed. The patient must be well hydrated. Children The recommendation of the Paediatric Task Group of the European Association of Nuclear Medicine (EANM) of 1990 lists the paediatric dose scaled to body weight as a fraction of the adult dose:
Parenteral drug products should be inspected visually for particulate matter and discoloration prior to administration. |  |  |  |  |  |  |  |  |  |  |  | 3 kg = 0.1 |  | 22 kg = 0.50 |  | 42 kg = 0.78
Parenteral drug products should be inspected visually for particulate matter and discoloration prior to administration. |  |  |  |  |  |  |  |  |  |  |  | 4 kg = 0.14 |  | 24 kg = 0.53 |  | 44 kg = 0.80
 |  |  |  |  |  |  |  |  |  |  |  | 6 kg = 0.19 |  | 26 kg = 0.56 |  | 46 kg = 0.82
 |  |  |  |  |  |  |  |  |  |  |  | 8 kg = 0.23 |  | 28 kg = 0.58 |  | 48 kg = 0.85
 |  |  |  |  |  |  |  |  |  |  |  | 10 kg = 0.27 |  | 30 kg = 0.62 |  | 50 kg = 0.88
 |  |  |  |  |  |  |  |  |  |  |  | 12 kg = 0.32 |  | 32 kg = 0.65 |  | 52 - 54 kg = 0.90
 |  |  |  |  |  |  |  |  |  |  |  | 14 kg = 0.36 |  | 34 kg = 0.68 |  | 56 - 58 kg = 0.92
 |  |  |  |  |  |  |  |  |  | Insert layout and details specific to manufacturer |  | 16 kg = 0.40 |  | 36 kg = 0.71 |  | 60 - 62 kg = 0.96
 |  |  |  |  |  |  |  |  |  | Insert layout and details specific to manufacturer |  | 18 kg = 0.44 |  | 38 kg = 0.73 |  | 64 - 66 kg = 0.98
 |  |  |  |  |  |  |  |  |  |  |  | 20 kg = 0.46 |  | 40 kg = 0.76 |  | 68 kg = 0.99
WARNINGS None. ADVERSE REACTIONS Rare instances of syncope, fever, nausea and maculopapular skin rash have been reported. CONTRAINDICATIONS None known. |  |  |  |  |  |  |  |  |  |  | Activity of less than 20 % (15 MBq) of the adult dose generally does not allow a satisfactory assessment to be derived from the examination. If you use more ROTOP – DMSA than you should Due to the low amounts of substances used, overdosage in the pharmacological sense is not expected. Exposure to radiation resulting from an overdosage of radioactivity can be reduced by forced diuresis. 4. POSSIBLE SIDE EFFECTS As all medicinal products, ROTOP - DMSA can cause side effects, although not everybody gets them. For assessing the side effects the frequency is classified as follows:
 |  |  |  |  |  |  |  |  |  |  |  | Very common |  | observed in more than 1 patients in 10
 |  |  |  |  |  |  |  |  |  |  |  | Common |  | observed in less than 1 patient in 10, but more than 1 patient in 100
 |  |  |  |  |  |  |  |  |  |  |  | Uncommon |  | observed in less than 1 patient in 100, but more than 1 patient in 1,000
 |  |  |  |  |  |  |  |  |  |  |  | Rare |  | observed in less than 1 patient in 1,000, but more than 1 patient in 10,000
 |  |  |  |  |  |  |  |  |  |  |  | Very rare |  | observed in less than 1 patient in 10,000 or not known
 |  |  |  |  |  |  |  |  |  |  | In very rare cases (< 0.01 %) after intravenous injection of the ready-to-use solution, hypersensitivity reactions have occurred such as locally confined or general rashes, itching, drop in blood pressure, headache, dizziness, nausea and vomiting. Reactions can occur up to 24 hours after the injection. Although such reactions are very rare and usually very minor, appropriate instruments and medications for immediate treatment of allergic reactions (adrenaline, corticosteroids and antihistamines) should be within reach for possible emergency treatment at all times.
 |  |  |  |  |  |  |  |  |  | Insert layout and details specific to manufacturer | Since the administered amounts of active substances are very low, the risks of use are mainly related to radiation exposure. Ionising radiation can cause cancer and genetic mutations. Since most radiopharmaceutical examinations are conducted with low effective radiation doses of less than 20 mSv, the probability of such effects occurring is expected to be low.
HOW SUPPLIED Kit Contents 5 Vials containing a freeze-dried mixture of 1.0 mg dimercaptosuccinic acid, 0.42 mg stannous chloride dihydrate [0.38 mg (minimum) stannous chloride dihydrate (SnCl2∙2H2O) and 0.46 mg (maximum) total tin expressed as stannous chloride dihydrate (SnCl2∙2H2O)], 0.70 mg ascorbic acid, and 50.0 mg inositol. 5 Labels 1 Package Insert |  |  |  |  |  |  |  |  |  |  | The effective radiation dose is 0.62 mSv when the maximum recommended activity of this medicinal product is applied. Reporting of side effects If you notice any side effects please contact your nuclear physician responsible for supervising the administration. This also applies to any side effects not listed in this leaflet. You can also report any side effects directly to: Bundesinstitut für Arzneimittel und Medizinprodukte, Abt. Pharmakovigilanz, Kurt-Georg-Kiesinger Allee 3, D-53175 Bonn, website: http://www.bfarm.de. By reporting side effects you can help provide more information on the safety of this medicine. 5. HOW TO STORE ROTOP - DMSA Keep out of the reach and sight of children. Do not use this medicinal product after the expiry date stated on the label.
NDC 017156-525-01 Storage Store the kit at 2°-8°C (36°-46°F) and protect from light. |  |  |  |  |  |  |  |  |  |  | Storage conditions Store refrigerated (2 to 8 °C) in the original package. Radiopharmaceuticals must be stored in accordance with the regulations for radioactive protection and in particular be kept from unauthorised access. Shelf life after opening and reconstitution The product labelled with [99mTc]technetium can be injected within 4 hours after reconstitution and has to be stored at room temperature (15–25 °C) during this time. 6. FURTHER INFORMATION What ROTOP – DMSA contains One vial contains 1.74 mg powder with the active substance: 1.0 mg succimer
This reagent kit is approved for use by persons licensed by the Illinois Emergency Management Agency pursuant to 32 Ill. Code Adm. Section, Section 330.260(a) and 335.4010 or under equivalent licenses of the U.S. Nuclear Regulatory Commission, or an Agreement State. |  |  |  |  |  |  |  |  |  | Insert layout and details specific to manufacturer | The other ingredients are: Stannous chloride dihydrate Ascorbic acid Sodium hydroxide Hydrochloric acid 36% Nitrogen
Manufactured for: GE Healthcare Medi-Physics, Inc. 3350 North Ridge Avenue Arlington Heights, IL 60004 1-800-633-4123 (Toll Free) By: GE Healthcare Ltd. Little Chalfont, HP7 9NA, UK GE and the GE Monogram are trademarks of General Electric Company. 43-4349H L/2331/04 Revised February 2006 |  |  |  |  |  |  |  |  |  |  | What ROTOP – DMSA looks like and contents of the pack: The package consists of a carton with 5 vials. Marketing Authorisation Holder and Manufacturer ROTOP Pharmaka GmbH, Bautzner Landstr. 400, 01328 Dresden, Germany Tel: 0049 + (0) 351 – 26 310 210 Fax: 0049 + (0) 351 – 26 310 313 e-mail: service@rotop-pharmaka.de This medicinal product is authorised in the Member States of the EEA under the following names:
 |  |  |  |  |  |  |  |  |  |  | Germany: |  |  | ROTOP - DMSA
CLINICAL PHARMACOLOGY |  |  |  |  |  |  |  |  |  |  | This leaflet was last approved in May 2017.
After intravenous administration, technetium Tc99m succimer injection is distributed in the plasma, apparently bound to plasma proteins.
There is negligible activity in the red blood cells. The activity is cleared from the plasma with a half-time of about 60 minutes and concentrates in the renal cortex. Approximately 16% of the activity is excreted in the urine within two hours. At six hours about 20% of the dose is concentrated in each kidney. |  |  |  |  |  |  |  |  |  |  | The following information is intended for medical or healthcare professionals only:
EXTERNAL RADIATION The specific gamma ray constant for technetium Tc99m is 0.78 R/hr-mCi at 1 cm. The first half value layer is 0.017 cm of Pb. To facilitate control of the radiation exposure from millicurie amounts of this radionuclide, the use of a 0.25 cm thickness of Pb will attenuate the radiation emitted by a factor of about 1,000. |  |  |  |  |  |  |  |  |  |  | PHARMACOLOGICAL PROPERTIES Pharmacodynamic properties Pharmacotherapeutic group: Diagnostic radiopharmaceutical for renal diagnostics (ATC: V09CA02). Based on current research, for the low amounts of substances used for imaging techniques no clinically relevant pharmacodynamic effects of [99mTc]DMSA are expected.
 |  | Table 2. Radiation Attenuation by Lead Shielding |  |  |  |  |  |  |  |  | Pharmacokinetic properties After intravenous injection, within 5 minutes over 70% of the [99mTc]DMSA is bound to theα-2 microglobulin fraction in blood plas ma. Binding to erythrocytes may be disregarded. One hour post injection, 25% of the radiopharmaceutical is already located in the renal cortex and only 30% remains in the plasma. Approx. 10% appears in the urine. In healthy persons, the plasma clearance of [99mTc]DMSA amounts to approx. 10 ml/min. (scaled to 1.73 sqm body surface). After approx. 3 hours, the maximum renal accumulation is reached. In healthy persons, at this point approx. 50% of the radiopharmaceutical is located in the renal cortex, approx. 20% remains in the plasma and just under 10% in the liver and muscles. Within 24 hours, approx. 30% is excreted with the urine.
 |  | Shield Thickness (Pb) cm |  |  |  | Coefficient of Attenuation |  |  |  |  | Pharmacokinetic properties After intravenous injection, within 5 minutes over 70% of the [99mTc]DMSA is bound to theα-2 microglobulin fraction in blood plas ma. Binding to erythrocytes may be disregarded. One hour post injection, 25% of the radiopharmaceutical is already located in the renal cortex and only 30% remains in the plasma. Approx. 10% appears in the urine. In healthy persons, the plasma clearance of [99mTc]DMSA amounts to approx. 10 ml/min. (scaled to 1.73 sqm body surface). After approx. 3 hours, the maximum renal accumulation is reached. In healthy persons, at this point approx. 50% of the radiopharmaceutical is located in the renal cortex, approx. 20% remains in the plasma and just under 10% in the liver and muscles. Within 24 hours, approx. 30% is excreted with the urine.
 |  | 0.02 |  |  |  | 0.5 |  |  |  | Insert layout and details specific to manufacturer | Pharmacokinetic properties After intravenous injection, within 5 minutes over 70% of the [99mTc]DMSA is bound to theα-2 microglobulin fraction in blood plas ma. Binding to erythrocytes may be disregarded. One hour post injection, 25% of the radiopharmaceutical is already located in the renal cortex and only 30% remains in the plasma. Approx. 10% appears in the urine. In healthy persons, the plasma clearance of [99mTc]DMSA amounts to approx. 10 ml/min. (scaled to 1.73 sqm body surface). After approx. 3 hours, the maximum renal accumulation is reached. In healthy persons, at this point approx. 50% of the radiopharmaceutical is located in the renal cortex, approx. 20% remains in the plasma and just under 10% in the liver and muscles. Within 24 hours, approx. 30% is excreted with the urine.
 |  | 0.08 |  |  |  | 0.1 |  |  |  | Insert layout and details specific to manufacturer | Pharmacokinetic properties After intravenous injection, within 5 minutes over 70% of the [99mTc]DMSA is bound to theα-2 microglobulin fraction in blood plas ma. Binding to erythrocytes may be disregarded. One hour post injection, 25% of the radiopharmaceutical is already located in the renal cortex and only 30% remains in the plasma. Approx. 10% appears in the urine. In healthy persons, the plasma clearance of [99mTc]DMSA amounts to approx. 10 ml/min. (scaled to 1.73 sqm body surface). After approx. 3 hours, the maximum renal accumulation is reached. In healthy persons, at this point approx. 50% of the radiopharmaceutical is located in the renal cortex, approx. 20% remains in the plasma and just under 10% in the liver and muscles. Within 24 hours, approx. 30% is excreted with the urine.
 |  | 0.16 |  |  |  | 0.01 |  |  |  | Insert layout and details specific to manufacturer | Pharmacokinetic properties After intravenous injection, within 5 minutes over 70% of the [99mTc]DMSA is bound to theα-2 microglobulin fraction in blood plas ma. Binding to erythrocytes may be disregarded. One hour post injection, 25% of the radiopharmaceutical is already located in the renal cortex and only 30% remains in the plasma. Approx. 10% appears in the urine. In healthy persons, the plasma clearance of [99mTc]DMSA amounts to approx. 10 ml/min. (scaled to 1.73 sqm body surface). After approx. 3 hours, the maximum renal accumulation is reached. In healthy persons, at this point approx. 50% of the radiopharmaceutical is located in the renal cortex, approx. 20% remains in the plasma and just under 10% in the liver and muscles. Within 24 hours, approx. 30% is excreted with the urine.
 |  | 0.25 |  |  |  | 0.001 |  |  |  |  | Pharmacokinetic properties After intravenous injection, within 5 minutes over 70% of the [99mTc]DMSA is bound to theα-2 microglobulin fraction in blood plas ma. Binding to erythrocytes may be disregarded. One hour post injection, 25% of the radiopharmaceutical is already located in the renal cortex and only 30% remains in the plasma. Approx. 10% appears in the urine. In healthy persons, the plasma clearance of [99mTc]DMSA amounts to approx. 10 ml/min. (scaled to 1.73 sqm body surface). After approx. 3 hours, the maximum renal accumulation is reached. In healthy persons, at this point approx. 50% of the radiopharmaceutical is located in the renal cortex, approx. 20% remains in the plasma and just under 10% in the liver and muscles. Within 24 hours, approx. 30% is excreted with the urine.
 |  | 0.33 |  |  |  | 0.0001 |  |  |  |  | Pharmacokinetic properties After intravenous injection, within 5 minutes over 70% of the [99mTc]DMSA is bound to theα-2 microglobulin fraction in blood plas ma. Binding to erythrocytes may be disregarded. One hour post injection, 25% of the radiopharmaceutical is already located in the renal cortex and only 30% remains in the plasma. Approx. 10% appears in the urine. In healthy persons, the plasma clearance of [99mTc]DMSA amounts to approx. 10 ml/min. (scaled to 1.73 sqm body surface). After approx. 3 hours, the maximum renal accumulation is reached. In healthy persons, at this point approx. 50% of the radiopharmaceutical is located in the renal cortex, approx. 20% remains in the plasma and just under 10% in the liver and muscles. Within 24 hours, approx. 30% is excreted with the urine.
To correct for physical decay of this radionuclide, the fractions that remain at selected intervals after the time of calibration are shown in Table 3. |  |  |  |  |  |  |  |  |  |  | Pharmacokinetic properties After intravenous injection, within 5 minutes over 70% of the [99mTc]DMSA is bound to theα-2 microglobulin fraction in blood plas ma. Binding to erythrocytes may be disregarded. One hour post injection, 25% of the radiopharmaceutical is already located in the renal cortex and only 30% remains in the plasma. Approx. 10% appears in the urine. In healthy persons, the plasma clearance of [99mTc]DMSA amounts to approx. 10 ml/min. (scaled to 1.73 sqm body surface). After approx. 3 hours, the maximum renal accumulation is reached. In healthy persons, at this point approx. 50% of the radiopharmaceutical is located in the renal cortex, approx. 20% remains in the plasma and just under 10% in the liver and muscles. Within 24 hours, approx. 30% is excreted with the urine.
 |  | Table 3. Physical Decay Chart: Tc99m, half-life 6.02 hours |  |  |  |  |  |  |  |  | [99mTc]DMSA accumulates in the pars recta and convoluta of the proximal renal tubules – most likely due to peritubular reabsorption. On an intracellular level, the majority of the [99mTc]DMSA is bound to a soluble protein in the cytosol. This mechanism, which has not yet been explained in detail, is disrupted in the case of proximal tubulopathies (such as nephritides or the Fanconi syndrome), which can be recognised by the increased plasma clearance of [99mTc]DMSA and low renal accumulation.
 |  | Hours | Fraction Remaining |  | Hours | Fraction Remaining |  |  |  |  | [99mTc]DMSA accumulates in the pars recta and convoluta of the proximal renal tubules – most likely due to peritubular reabsorption. On an intracellular level, the majority of the [99mTc]DMSA is bound to a soluble protein in the cytosol. This mechanism, which has not yet been explained in detail, is disrupted in the case of proximal tubulopathies (such as nephritides or the Fanconi syndrome), which can be recognised by the increased plasma clearance of [99mTc]DMSA and low renal accumulation.
 |  | 0* | 1.000 |  | 7 | 0.447 |  |  |  |  | [99mTc]DMSA accumulates in the pars recta and convoluta of the proximal renal tubules – most likely due to peritubular reabsorption. On an intracellular level, the majority of the [99mTc]DMSA is bound to a soluble protein in the cytosol. This mechanism, which has not yet been explained in detail, is disrupted in the case of proximal tubulopathies (such as nephritides or the Fanconi syndrome), which can be recognised by the increased plasma clearance of [99mTc]DMSA and low renal accumulation.
 |  | 1 | 0.891 |  | 8 | 0.398 |  |  |  |  | [99mTc]DMSA accumulates in the pars recta and convoluta of the proximal renal tubules – most likely due to peritubular reabsorption. On an intracellular level, the majority of the [99mTc]DMSA is bound to a soluble protein in the cytosol. This mechanism, which has not yet been explained in detail, is disrupted in the case of proximal tubulopathies (such as nephritides or the Fanconi syndrome), which can be recognised by the increased plasma clearance of [99mTc]DMSA and low renal accumulation.
 |  | 2 | 0.794 |  | 9 | 0.355 |  |  |  |  | [99mTc]DMSA accumulates in the pars recta and convoluta of the proximal renal tubules – most likely due to peritubular reabsorption. On an intracellular level, the majority of the [99mTc]DMSA is bound to a soluble protein in the cytosol. This mechanism, which has not yet been explained in detail, is disrupted in the case of proximal tubulopathies (such as nephritides or the Fanconi syndrome), which can be recognised by the increased plasma clearance of [99mTc]DMSA and low renal accumulation.
 |  | 3 | 0.708 |  | 10 | 0.316 |  |  |  |  | [99mTc]DMSA accumulates in the pars recta and convoluta of the proximal renal tubules – most likely due to peritubular reabsorption. On an intracellular level, the majority of the [99mTc]DMSA is bound to a soluble protein in the cytosol. This mechanism, which has not yet been explained in detail, is disrupted in the case of proximal tubulopathies (such as nephritides or the Fanconi syndrome), which can be recognised by the increased plasma clearance of [99mTc]DMSA and low renal accumulation.
 |  | 4 | 0.631 |  | 11 | 0.282 |  |  |  |  | [99mTc]DMSA accumulates in the pars recta and convoluta of the proximal renal tubules – most likely due to peritubular reabsorption. On an intracellular level, the majority of the [99mTc]DMSA is bound to a soluble protein in the cytosol. This mechanism, which has not yet been explained in detail, is disrupted in the case of proximal tubulopathies (such as nephritides or the Fanconi syndrome), which can be recognised by the increased plasma clearance of [99mTc]DMSA and low renal accumulation.
 |  | 5 | 0.562 |  | 12 | 0.251 |  |  |  |  | [99mTc]DMSA accumulates in the pars recta and convoluta of the proximal renal tubules – most likely due to peritubular reabsorption. On an intracellular level, the majority of the [99mTc]DMSA is bound to a soluble protein in the cytosol. This mechanism, which has not yet been explained in detail, is disrupted in the case of proximal tubulopathies (such as nephritides or the Fanconi syndrome), which can be recognised by the increased plasma clearance of [99mTc]DMSA and low renal accumulation.
 |  | 6 | 0.501 |  |  |  |  |  |  |  | [99mTc]DMSA accumulates in the pars recta and convoluta of the proximal renal tubules – most likely due to peritubular reabsorption. On an intracellular level, the majority of the [99mTc]DMSA is bound to a soluble protein in the cytosol. This mechanism, which has not yet been explained in detail, is disrupted in the case of proximal tubulopathies (such as nephritides or the Fanconi syndrome), which can be recognised by the increased plasma clearance of [99mTc]DMSA and low renal accumulation.
 |  | * Calibration Time |  |  |  |  |  |  |  |  | [99mTc]DMSA accumulates in the pars recta and convoluta of the proximal renal tubules – most likely due to peritubular reabsorption. On an intracellular level, the majority of the [99mTc]DMSA is bound to a soluble protein in the cytosol. This mechanism, which has not yet been explained in detail, is disrupted in the case of proximal tubulopathies (such as nephritides or the Fanconi syndrome), which can be recognised by the increased plasma clearance of [99mTc]DMSA and low renal accumulation.
DISPOSAL Any unused portion of the Tc99m-labeled kit must be stored and disposed of in accordance with the conditions of NRC radioactive materials license pursuant to 10 CFR Parts 20 and 35 or equivalent conditions pursuant to Agreement state regulation, or other regulatory agency authorized to license the use of radionuclides. The unlabeled residual materials may be discarded in ordinary trash, provided that the vials and syringes read background with an appropriate low-range survey meter. It is suggested that all identification labels be destroyed before discarding. RADIATION DOSIMETRY The estimated absorbed radiation doses^2,3 to an average adult (70 kg) are shown in Table 4. |  |  |  |  |  |  |  |  |  |  | Toxicological properties Due to the low amounts of DMSA and stannous chloride contained in the kit, toxic effects brought about by the substances are not expected if used according to directions. Data on investigations on reproduction toxicity as well as on mutagenicity and cancerogenity are not available. Special precautions for disposal and further directions for handling The empty package is considered to be regular waste if the permitted level for [99mTc]technetium is not exceeded (≤ 0.5 Bq/g or 0.5 Bq/cm^2). Particulars indicating radioactivity must be removed prior to disposing of the non-radioactive waste and must be destroyed separately. Radioactive waste must be disposed of as provided by law. MARKETING AUTHORISATION NUMBER 3003663.00.00 DATE OF FIRST AUTHORISATION/ RENEWAL OF THE AUTHORISATION 24/11/2005
 | Table 4. Absorbed Radiation Dose |  |  |  |  |  |  |  |  | Insert layout and details specific to manufacturer | DOSIMETRY Radiation exposure According ICRP publication 80 (Table 1) the following radiation doses will be absorbed:
 | Tissue |  |  | mGy / 222 MBq |  | rads / 6 mCi |  |  |  | Insert layout and details specific to manufacturer | DOSIMETRY Radiation exposure According ICRP publication 80 (Table 1) the following radiation doses will be absorbed:
 | Bladder Wall |  |  | 4.2 |  | 0.42 |  |  |  | Insert layout and details specific to manufacturer | DOSIMETRY Radiation exposure According ICRP publication 80 (Table 1) the following radiation doses will be absorbed:
 | Kidneys (total) |  |  | 37.8 |  | 3.78 |  |  |  | Insert layout and details specific to manufacturer | DOSIMETRY Radiation exposure According ICRP publication 80 (Table 1) the following radiation doses will be absorbed:
 | Renal Cortices |  |  | 51.0 |  | 5.10 |  |  |  | Insert layout and details specific to manufacturer | DOSIMETRY Radiation exposure According ICRP publication 80 (Table 1) the following radiation doses will be absorbed:
 | Liver |  |  | 1.9 |  | 0.19 |  |  |  | Insert layout and details specific to manufacturer | DOSIMETRY Radiation exposure According ICRP publication 80 (Table 1) the following radiation doses will be absorbed:
 | Bone Marrow |  |  | 1.3 |  | 0.13 |  |  |  | Insert layout and details specific to manufacturer | DOSIMETRY Radiation exposure According ICRP publication 80 (Table 1) the following radiation doses will be absorbed:
 | Ovaries |  |  | 0.8 |  | 0.08
 | Testes |  |  | 0.4 |  | 0.04
 | Total Body |  |  | 0.9 |  | 0.09
 |  |  |  |  |  |  |  |  |  |  |  | Absorbed dose per unit of activity administered (mGy/MBq)
^2 Method of Calculation: A schema for Absorbed-Dose Calculations for Biologically Distributed Radionuclides, Supplement No. 1, MIRD Pamphlet No. 1, J. Nucl. Med., p. 7, 1968. ^3 Biological Data: Arnold, R.W; Subramanian, G.; McAfee, J.G.; Blair, R.J.; Thomas, F.D.; Comparison of Tc99m complexes for renal imaging, J. Nucl. Med., 16, pp. 357-367, 1975. |  |  |  |  |  |  |  |  |  |  |  | Organ | Adults | 15 years | 10 years | 5 years | 1 year
^2 Method of Calculation: A schema for Absorbed-Dose Calculations for Biologically Distributed Radionuclides, Supplement No. 1, MIRD Pamphlet No. 1, J. Nucl. Med., p. 7, 1968. ^3 Biological Data: Arnold, R.W; Subramanian, G.; McAfee, J.G.; Blair, R.J.; Thomas, F.D.; Comparison of Tc99m complexes for renal imaging, J. Nucl. Med., 16, pp. 357-367, 1975. |  |  |  |  |  |  |  |  |  |  |  | Adrenals | 0.012 | 0.016 | 0.024 | 0.035 | 0.060
^2 Method of Calculation: A schema for Absorbed-Dose Calculations for Biologically Distributed Radionuclides, Supplement No. 1, MIRD Pamphlet No. 1, J. Nucl. Med., p. 7, 1968. ^3 Biological Data: Arnold, R.W; Subramanian, G.; McAfee, J.G.; Blair, R.J.; Thomas, F.D.; Comparison of Tc99m complexes for renal imaging, J. Nucl. Med., 16, pp. 357-367, 1975. |  |  |  |  |  |  |  |  |  |  |  | Bladders wall | 0.018 | 0.023 | 0.029 | 0.031 | 0.057
^2 Method of Calculation: A schema for Absorbed-Dose Calculations for Biologically Distributed Radionuclides, Supplement No. 1, MIRD Pamphlet No. 1, J. Nucl. Med., p. 7, 1968. ^3 Biological Data: Arnold, R.W; Subramanian, G.; McAfee, J.G.; Blair, R.J.; Thomas, F.D.; Comparison of Tc99m complexes for renal imaging, J. Nucl. Med., 16, pp. 357-367, 1975. |  |  |  |  |  |  |  |  |  |  |  | Bone surface | 0.0050 | 0.0062 | 0.0092 | 0.014 | 0.026
^2 Method of Calculation: A schema for Absorbed-Dose Calculations for Biologically Distributed Radionuclides, Supplement No. 1, MIRD Pamphlet No. 1, J. Nucl. Med., p. 7, 1968. ^3 Biological Data: Arnold, R.W; Subramanian, G.; McAfee, J.G.; Blair, R.J.; Thomas, F.D.; Comparison of Tc99m complexes for renal imaging, J. Nucl. Med., 16, pp. 357-367, 1975. |  |  |  |  |  |  |  |  |  |  |  | Brain | 0.0012 | 0.0015 | 0.0025 | 0.0040 | 0.0072
^2 Method of Calculation: A schema for Absorbed-Dose Calculations for Biologically Distributed Radionuclides, Supplement No. 1, MIRD Pamphlet No. 1, J. Nucl. Med., p. 7, 1968. ^3 Biological Data: Arnold, R.W; Subramanian, G.; McAfee, J.G.; Blair, R.J.; Thomas, F.D.; Comparison of Tc99m complexes for renal imaging, J. Nucl. Med., 16, pp. 357-367, 1975. |  |  |  |  |  |  |  |  |  |  |  | Breast | 0.0013 | 0.0018 | 0.0028 | 0.0045 | 0.0084
^2 Method of Calculation: A schema for Absorbed-Dose Calculations for Biologically Distributed Radionuclides, Supplement No. 1, MIRD Pamphlet No. 1, J. Nucl. Med., p. 7, 1968. ^3 Biological Data: Arnold, R.W; Subramanian, G.; McAfee, J.G.; Blair, R.J.; Thomas, F.D.; Comparison of Tc99m complexes for renal imaging, J. Nucl. Med., 16, pp. 357-367, 1975. |  |  |  |  |  |  |  |  |  |  |  | Gall bladder | 0.0083 | 0.010 | 0.014 | 0.022 | 0.031
^2 Method of Calculation: A schema for Absorbed-Dose Calculations for Biologically Distributed Radionuclides, Supplement No. 1, MIRD Pamphlet No. 1, J. Nucl. Med., p. 7, 1968. ^3 Biological Data: Arnold, R.W; Subramanian, G.; McAfee, J.G.; Blair, R.J.; Thomas, F.D.; Comparison of Tc99m complexes for renal imaging, J. Nucl. Med., 16, pp. 357-367, 1975. |  |  |  |  |  |  |  |  |  |  |  | Stomach wall | 0.0052 | 0.0063 | 0.010 | 0.014 | 0.020
^2 Method of Calculation: A schema for Absorbed-Dose Calculations for Biologically Distributed Radionuclides, Supplement No. 1, MIRD Pamphlet No. 1, J. Nucl. Med., p. 7, 1968. ^3 Biological Data: Arnold, R.W; Subramanian, G.; McAfee, J.G.; Blair, R.J.; Thomas, F.D.; Comparison of Tc99m complexes for renal imaging, J. Nucl. Med., 16, pp. 357-367, 1975. |  |  |  |  |  |  |  |  |  |  |  | Colon | 0.0050 | 0.0063 | 0.010 | 0.014 | 0.024
^2 Method of Calculation: A schema for Absorbed-Dose Calculations for Biologically Distributed Radionuclides, Supplement No. 1, MIRD Pamphlet No. 1, J. Nucl. Med., p. 7, 1968. ^3 Biological Data: Arnold, R.W; Subramanian, G.; McAfee, J.G.; Blair, R.J.; Thomas, F.D.; Comparison of Tc99m complexes for renal imaging, J. Nucl. Med., 16, pp. 357-367, 1975. |  |  |  |  |  |  |  |  |  |  |  | Intestine | 0.0043 | 0.0055 | 0.0082 | 0.012 | 0.020
^2 Method of Calculation: A schema for Absorbed-Dose Calculations for Biologically Distributed Radionuclides, Supplement No. 1, MIRD Pamphlet No. 1, J. Nucl. Med., p. 7, 1968. ^3 Biological Data: Arnold, R.W; Subramanian, G.; McAfee, J.G.; Blair, R.J.; Thomas, F.D.; Comparison of Tc99m complexes for renal imaging, J. Nucl. Med., 16, pp. 357-367, 1975. |  |  |  |  |  |  |  |  |  |  |  | Upper large intestine | 0.0050 | 0.0064 | 0.095 | 0.014 | 0.023
^2 Method of Calculation: A schema for Absorbed-Dose Calculations for Biologically Distributed Radionuclides, Supplement No. 1, MIRD Pamphlet No. 1, J. Nucl. Med., p. 7, 1968. ^3 Biological Data: Arnold, R.W; Subramanian, G.; McAfee, J.G.; Blair, R.J.; Thomas, F.D.; Comparison of Tc99m complexes for renal imaging, J. Nucl. Med., 16, pp. 357-367, 1975. |  |  |  |  |  |  |  |  |  |  |  | Lower large intestine | 0.0035 | 0.0043 | 0.0065 | 0.0096 | 0.016
^2 Method of Calculation: A schema for Absorbed-Dose Calculations for Biologically Distributed Radionuclides, Supplement No. 1, MIRD Pamphlet No. 1, J. Nucl. Med., p. 7, 1968. ^3 Biological Data: Arnold, R.W; Subramanian, G.; McAfee, J.G.; Blair, R.J.; Thomas, F.D.; Comparison of Tc99m complexes for renal imaging, J. Nucl. Med., 16, pp. 357-367, 1975. |  |  |  |  |  |  |  |  |  |  |  | Heart | 0.0030 | 0.0038 | 0.0058 | 0.0086 | 0.014
^2 Method of Calculation: A schema for Absorbed-Dose Calculations for Biologically Distributed Radionuclides, Supplement No. 1, MIRD Pamphlet No. 1, J. Nucl. Med., p. 7, 1968. ^3 Biological Data: Arnold, R.W; Subramanian, G.; McAfee, J.G.; Blair, R.J.; Thomas, F.D.; Comparison of Tc99m complexes for renal imaging, J. Nucl. Med., 16, pp. 357-367, 1975. |  |  |  |  |  |  |  |  |  |  |  | Kidneys | 0.18 | 0.22 | 0.30 | 0.43 | 0.76
^2 Method of Calculation: A schema for Absorbed-Dose Calculations for Biologically Distributed Radionuclides, Supplement No. 1, MIRD Pamphlet No. 1, J. Nucl. Med., p. 7, 1968. ^3 Biological Data: Arnold, R.W; Subramanian, G.; McAfee, J.G.; Blair, R.J.; Thomas, F.D.; Comparison of Tc99m complexes for renal imaging, J. Nucl. Med., 16, pp. 357-367, 1975. |  |  |  |  |  |  |  |  |  |  |  | Liver | 0.0095 | 0.012 | 0.018 | 0.025 | 0.041
^2 Method of Calculation: A schema for Absorbed-Dose Calculations for Biologically Distributed Radionuclides, Supplement No. 1, MIRD Pamphlet No. 1, J. Nucl. Med., p. 7, 1968. ^3 Biological Data: Arnold, R.W; Subramanian, G.; McAfee, J.G.; Blair, R.J.; Thomas, F.D.; Comparison of Tc99m complexes for renal imaging, J. Nucl. Med., 16, pp. 357-367, 1975. |  |  |  |  |  |  |  |  |  |  |  | Lungs | 0.0025 | 0.0035 | 0.0052 | 0.0080 | 0.015
^2 Method of Calculation: A schema for Absorbed-Dose Calculations for Biologically Distributed Radionuclides, Supplement No. 1, MIRD Pamphlet No. 1, J. Nucl. Med., p. 7, 1968. ^3 Biological Data: Arnold, R.W; Subramanian, G.; McAfee, J.G.; Blair, R.J.; Thomas, F.D.; Comparison of Tc99m complexes for renal imaging, J. Nucl. Med., 16, pp. 357-367, 1975. |  |  |  |  |  |  |  |  |  |  |  | Muscles | 0.0029 | 0.0036 | 0.0052 | 0.0077 | 0.014
^2 Method of Calculation: A schema for Absorbed-Dose Calculations for Biologically Distributed Radionuclides, Supplement No. 1, MIRD Pamphlet No. 1, J. Nucl. Med., p. 7, 1968. ^3 Biological Data: Arnold, R.W; Subramanian, G.; McAfee, J.G.; Blair, R.J.; Thomas, F.D.; Comparison of Tc99m complexes for renal imaging, J. Nucl. Med., 16, pp. 357-367, 1975. |  |  |  |  |  |  |  |  |  |  |  | Oesophagus | 0.0017 | 0.0023 | 0.0034 | 0.0054 | 0.0094
^2 Method of Calculation: A schema for Absorbed-Dose Calculations for Biologically Distributed Radionuclides, Supplement No. 1, MIRD Pamphlet No. 1, J. Nucl. Med., p. 7, 1968. ^3 Biological Data: Arnold, R.W; Subramanian, G.; McAfee, J.G.; Blair, R.J.; Thomas, F.D.; Comparison of Tc99m complexes for renal imaging, J. Nucl. Med., 16, pp. 357-367, 1975. |  |  |  |  |  |  |  |  |  |  |  | Ovaries | 0.0035 | 0.0047 | 0.0070 | 0.011 | 0.019
^2 Method of Calculation: A schema for Absorbed-Dose Calculations for Biologically Distributed Radionuclides, Supplement No. 1, MIRD Pamphlet No. 1, J. Nucl. Med., p. 7, 1968. ^3 Biological Data: Arnold, R.W; Subramanian, G.; McAfee, J.G.; Blair, R.J.; Thomas, F.D.; Comparison of Tc99m complexes for renal imaging, J. Nucl. Med., 16, pp. 357-367, 1975. |  |  |  |  |  |  |  |  |  |  |  | Pancreas | 0.0090 | 0.011 | 0.016 | 0.023 | 0.037
^2 Method of Calculation: A schema for Absorbed-Dose Calculations for Biologically Distributed Radionuclides, Supplement No. 1, MIRD Pamphlet No. 1, J. Nucl. Med., p. 7, 1968. ^3 Biological Data: Arnold, R.W; Subramanian, G.; McAfee, J.G.; Blair, R.J.; Thomas, F.D.; Comparison of Tc99m complexes for renal imaging, J. Nucl. Med., 16, pp. 357-367, 1975. |  |  |  |  |  |  |  |  |  |  |  | Red marrow | 0.0039 | 0.0047 | 0.0068 | 0.0090 | 0.014
^2 Method of Calculation: A schema for Absorbed-Dose Calculations for Biologically Distributed Radionuclides, Supplement No. 1, MIRD Pamphlet No. 1, J. Nucl. Med., p. 7, 1968. ^3 Biological Data: Arnold, R.W; Subramanian, G.; McAfee, J.G.; Blair, R.J.; Thomas, F.D.; Comparison of Tc99m complexes for renal imaging, J. Nucl. Med., 16, pp. 357-367, 1975. |  |  |  |  |  |  |  |  |  |  |  | Skin | 0.0015 | 0.0018 | 0.0029 | 0.0045 | 0.0085
^2 Method of Calculation: A schema for Absorbed-Dose Calculations for Biologically Distributed Radionuclides, Supplement No. 1, MIRD Pamphlet No. 1, J. Nucl. Med., p. 7, 1968. ^3 Biological Data: Arnold, R.W; Subramanian, G.; McAfee, J.G.; Blair, R.J.; Thomas, F.D.; Comparison of Tc99m complexes for renal imaging, J. Nucl. Med., 16, pp. 357-367, 1975. |  |  |  |  |  |  |  |  |  |  |  | Spleen | 0.013 | 0.017 | 0.026 | 0.038 | 0.061
^2 Method of Calculation: A schema for Absorbed-Dose Calculations for Biologically Distributed Radionuclides, Supplement No. 1, MIRD Pamphlet No. 1, J. Nucl. Med., p. 7, 1968. ^3 Biological Data: Arnold, R.W; Subramanian, G.; McAfee, J.G.; Blair, R.J.; Thomas, F.D.; Comparison of Tc99m complexes for renal imaging, J. Nucl. Med., 16, pp. 357-367, 1975. |  |  |  |  |  |  |  |  |  |  |  | Testes | 0.0018 | 0.0024 | 0.0037 | 0.0053 | 0.010
^2 Method of Calculation: A schema for Absorbed-Dose Calculations for Biologically Distributed Radionuclides, Supplement No. 1, MIRD Pamphlet No. 1, J. Nucl. Med., p. 7, 1968. ^3 Biological Data: Arnold, R.W; Subramanian, G.; McAfee, J.G.; Blair, R.J.; Thomas, F.D.; Comparison of Tc99m complexes for renal imaging, J. Nucl. Med., 16, pp. 357-367, 1975. |  |  |  |  |  |  |  |  |  |  |  | Thymus | 0.0017 | 0.0023 | 0.0034 | 0.0054 | 0.0094
^2 Method of Calculation: A schema for Absorbed-Dose Calculations for Biologically Distributed Radionuclides, Supplement No. 1, MIRD Pamphlet No. 1, J. Nucl. Med., p. 7, 1968. ^3 Biological Data: Arnold, R.W; Subramanian, G.; McAfee, J.G.; Blair, R.J.; Thomas, F.D.; Comparison of Tc99m complexes for renal imaging, J. Nucl. Med., 16, pp. 357-367, 1975. |  |  |  |  |  |  |  |  |  |  |  | Thyroid | 0.0015 | 0.0019 | 0.0031 | 0.0052 | 0.0094
^2 Method of Calculation: A schema for Absorbed-Dose Calculations for Biologically Distributed Radionuclides, Supplement No. 1, MIRD Pamphlet No. 1, J. Nucl. Med., p. 7, 1968. ^3 Biological Data: Arnold, R.W; Subramanian, G.; McAfee, J.G.; Blair, R.J.; Thomas, F.D.; Comparison of Tc99m complexes for renal imaging, J. Nucl. Med., 16, pp. 357-367, 1975. |  |  |  |  |  |  |  |  |  |  |  | Uterus | 0.0045 | 0.0056 | 0.0083 | 0.011 | 0.019
^2 Method of Calculation: A schema for Absorbed-Dose Calculations for Biologically Distributed Radionuclides, Supplement No. 1, MIRD Pamphlet No. 1, J. Nucl. Med., p. 7, 1968. ^3 Biological Data: Arnold, R.W; Subramanian, G.; McAfee, J.G.; Blair, R.J.; Thomas, F.D.; Comparison of Tc99m complexes for renal imaging, J. Nucl. Med., 16, pp. 357-367, 1975. |  |  |  |  |  |  |  |  |  |  |  | Remaining organ | 0.0029 | 0.0037 | 0.0052 | 0.0077 | 0.014
^2 Method of Calculation: A schema for Absorbed-Dose Calculations for Biologically Distributed Radionuclides, Supplement No. 1, MIRD Pamphlet No. 1, J. Nucl. Med., p. 7, 1968. ^3 Biological Data: Arnold, R.W; Subramanian, G.; McAfee, J.G.; Blair, R.J.; Thomas, F.D.; Comparison of Tc99m complexes for renal imaging, J. Nucl. Med., 16, pp. 357-367, 1975. |  |  |  |  |  |  |  |  |  | Insert layout and details specific to manufacturer |  | Effective Dose per unit of activity administered (mSv/MBq) | 0.0088 | 0.011 | 0.015 | 0.021 | 0.037
 |  |  |  |  |  |  |  |  |  |  | In an adult (70 kg), after intravenous injection of 70 MBq (maximum dose) [99mTc]DMSA, the effective dose is approx. 0.62 mSv. The absorbed dose in the target organ kidney is approx. 12.6 mGy and in the critical organ bladder wall 1.26 mGy.
 |  |  |  |  |  |  |  |  |  |  | Radiophysical Properties
Preparation The following directions must be carefully followed for optimum preparation of technetium Tc99m succimer injection: Note: Use aseptic procedures throughout and take precautions to minimize radiation exposure by the use of suitable shielding. Waterproof gloves should be worn during the preparation procedure.; 1. Place one of the vials in a suitable shielding container and swab the closure with a bacteriostatic swab. 2. Using a 10 mL sterile syringe, inject an appropriate amount (see notes 1 and 2) of the eluate from a Tc99m generator into the shielded vial. Before removing the syringe from the vial withdraw an equivalent volume of nitrogen from the space above the solution to normalize the pressure in the vial. 3. Carefully invert the vial a few times until the powder is completely dissolved. 4. Assay the total activity, complete the label provided and attach to the vial. 5. Incubate the vial for at least 10 minutes at room temperature. 6. Use the preparation between 10 minutes and 4 hours following reconstitution.; Note:; 1. Not more than 1.48 GBq, 40 mCi technetium-99m in a volume of 1-6 mL should be added to the vial. 2. Before reconstitution, the eluate may be adjusted to the correct radioactive concentration by dilution with preservative-free, non-bacteriostatic saline for injection. 3. The use of technetium-99m solution complying with the specifications prescribed by the USP Monograph on Sodium Pertechnetate (99mTc) injection will yield a preparation of an appropriate quality. 4. It is recommended that with proper shielding and equipment, the final formulation be tested for radiochemical purity. If radiochemical purity is not adequate, discard the finished drug. |  |  |  |  |  |  |  |  |  | Insert layout and details specific to manufacturer | [99mTc]technetium is produced using a [^99Mo/99mTc] sterile generator and decays releasing gamma radiation with an energy of 140/142 keV with a half-life of 6.02 hours to [99Tc]technetium, which in turn decays to stable [^99Ru]ruthenium; However, due to a long half-life of 214,000 years, ^99Tc itself is considered to be stable. INSTRUCTIONS FOR PREPARATION OF RADIOPHARMACEUTICALS Instruction for labelling [99mTc]technetium succimer injection solution is prepared under sterile conditions with a sodium [99mTc]pertechnetate injection solution (European Pharmacopoeia quality 4.00/0124 or 4.00/0283) directly before use. Oxygenation must be avoided. Place the vial with powder in sufficient lead shielding with ample space and disinfect the stopper (allow disinfectant to dry). Use a syringe with the smallest possible cannula lumen to transfer 5 mL sodium [99mTc]technetium pertechnetate solution with a maximum of 3 GBq to the vial. Use the same syringe to withdraw the appropriate gas volume from the vial for pressure compensation. Lightly shake the vial in order to completely dissolve the powder. The stopper should be well moistened as well. After 10 minutes reaction time, measure the overall activity. If needed, the finished injection solution can be diluted with sterile isotonic sodium chloride to a total volume of up to 10 mL. Quality Control Prior to use in the patient, the radiochemical purity of the [99mTc]technetium succimer injection solution must be tested using the method described below:
Rx ONLY |  |  |  |  |  |  |  |  |  |  | Preparation: Type of test: Thin layer chromatography Plates used: Silica gel on a glass fibre plate, heated for 10 min. at 110 °C prior to testing Starting point: 1.5 cm from lower end of the plate Migration distance: 10 to 15 cm (in approx. 15 minutes) Execution: Use a capillary tube or pipette to extract a volume of approx. 5 μl and apply it to the plate. Chromatography begins immediately with a solution of methylethylketone (MEK) over a migration distance of 10 to 15 cm. Allow the plate to air-dry, and use a detector to determine the distribution of radioactivity. Evaluation: The [99mTc] technetium succimer complex remains at the starting point while [99mTc] pertechnetate migrates near the solvent front.
 |  |  |  |  |  |  |  |  |  |  | Target value: |  | ≥ 95.0 % [99mTc]technetium succimer
 |  |  |  |  |  |  |  |  |  |  |  |  | ≤ 2.0% [99mTc]pertechnetate
 |  |  |  |  |  |  |  |  |  |  | CLASSIFICATION FOR SUPPLY Pharmacy-only medicine

Attachment 3: Product Labels

Vial

Carton

PRINCIPAL DISPLAY PANEL - 1.74 mg Vial Label

ROTOP - DMSA 1,0 mg
Kit for radiopharmaceutical preparation

ROTOP

For the use in infants, children and adults.

For intravenous use after reconstitution and labelling.

1.74 mg powder for solution for injection.

Lot:

EXP:

PRINCIPAL DISPLAY PANEL - 5 Vial Carton Label

ROTOP – DMSA 1.0 mg
Kit for radiopharmaceutical preparation
Succimer

For the use in infants, children and adults.

5 vials

Content/vial:
1.74 mg powder for solution for injection
active substance: 1.0 mg succimer
excipients: stannous chloride dihydrate, ascorbic acid, sodium
hydroxide, hydrochloric acid, nitrogen

For intravenous use after reconstitution and labelling. Store in the original package in order
to protect from light. Store in a refrigerator at 2 – 8 °C. Keep out of the sight and reach of
children.

MA Number: 3003663.00.00
pharmacy only medicine

ROTOP Pharmaka GmbH, Bautzner Landstraẞe 400, 01328 Dresden, Germany

ROTOP